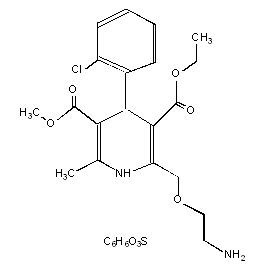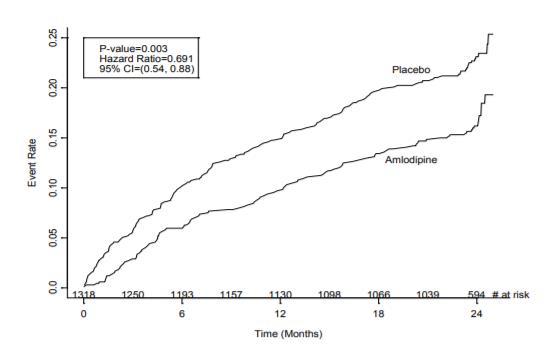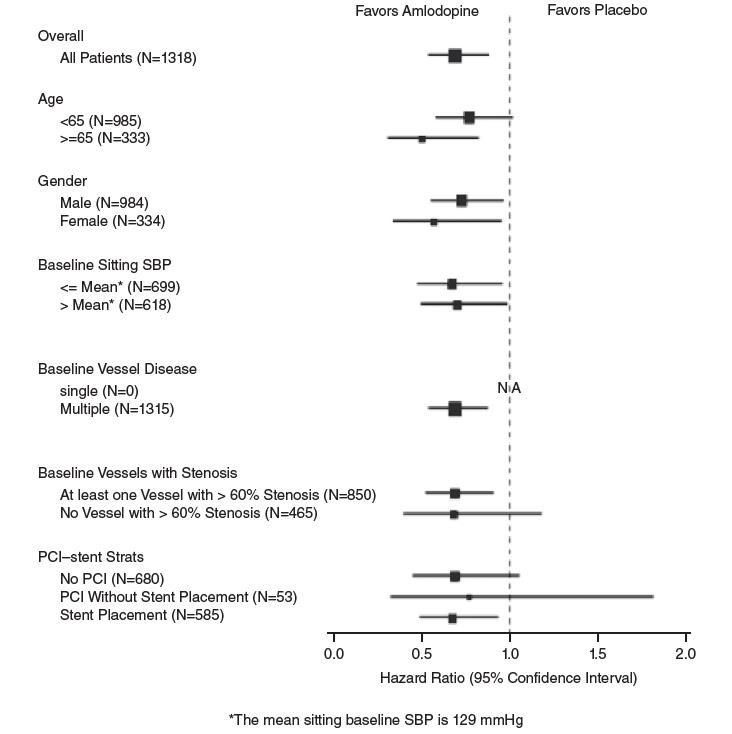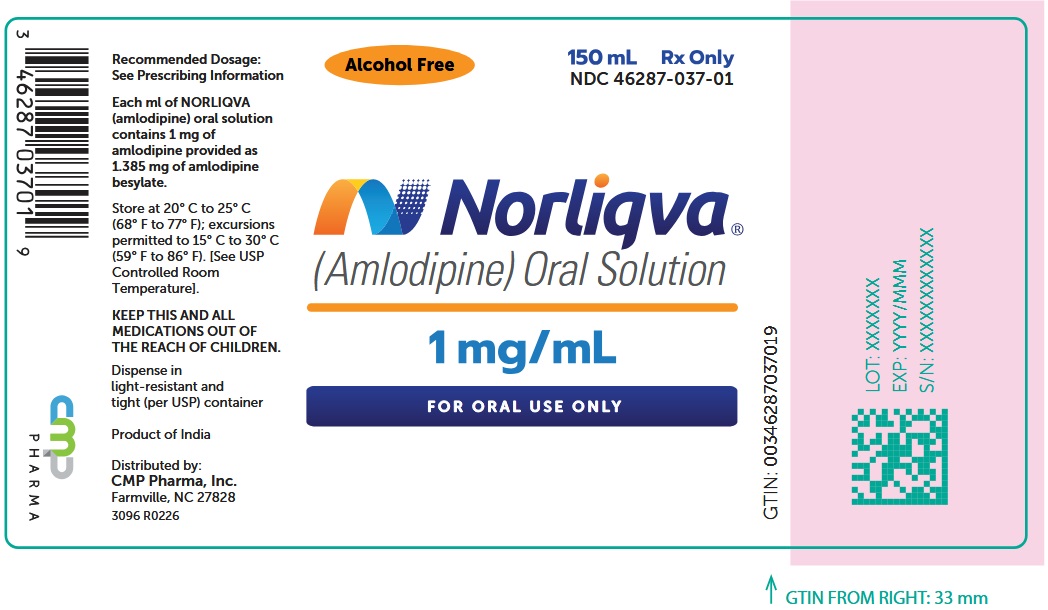 DRUG LABEL: NORLIQVA
NDC: 46287-037 | Form: Solution
Manufacturer: CMP Pharma, Inc.
Category: prescription | Type: HUMAN PRESCRIPTION DRUG LABEL
Date: 20260215

ACTIVE INGREDIENTS: amlodipine 1 mg/1 mL
INACTIVE INGREDIENTS: glycerin; propylene glycol; butylated hydroxyanisole

HIGHLIGHTS OF PRESCRIBING INFORMATION

These highlights do not include all the information needed to use NORLIQVA safely and effectively. See full prescribing information for NORLIQVA.
NORLIQVA® (amlodipine) oral solution
Initial U.S. Approval: 1992

1 INDICATIONS AND USAGE

NORLIQVA is a calcium channel blocker for the treatment of:

- Hypertension (1.1)
  - NORLIQVA is indicated for the treatment of hypertension in adults and children 6 years of age and older, to lower blood pressure. Lowering blood pressure reduces the risk of fatal and nonfatal cardiovascular events, primarily strokes and myocardial infarctions.
- Coronary Artery Disease (1.2)
  - Chronic Stable Angina
  - Vasospastic Angina (Prinzmetal's or Variant Angina)
  - Angiographically Documented Coronary Artery Disease in patients without heart failure or an ejection fraction <40%

2 DOSAGE AND ADMINISTRATION

- Adult recommended starting dose: 5 mg orally once daily with a maximum of 10 mg orally once daily. (2.1)
  - Small, fragile, or elderly patients, or patients with hepatic insufficiency may be started on 2.5 mg orally once daily. (2.1)
- Pediatric starting dose: 2.5 mg to 5 mg orally once daily. (2.2)

3 DOSAGE FORMS AND STRENGTHS

- Oral solution: 1 mg/mL (3)

4 CONTRAINDICATIONS

- Sensitivity to amlodipine (4)

5 WARNINGS AND PRECAUTIONS

- Symptomatic hypotension is possible, particularly in patients with severe aortic stenosis. However, acute hypotension is unlikely. (5.1)
- Worsening angina and acute myocardial infarction can develop after starting or increasing the dose of NORLIQVA, particularly in patients with severe obstructive coronary artery disease. (5.2)
- Titrate slowly in patients with severe hepatic impairment. (5.3)

6 ADVERSE REACTIONS

The most common adverse reactions are nausea, anorexia, and bloating. (6)

To report SUSPECTED ADVERSE REACTIONS, contact CMP Pharma, Inc. at 1-844-321-1443 or FDA at 1-800-FDA-1088 or www.fda.gov/medwatch.

7 DRUG INTERACTIONS

- Do not exceed doses greater than 20 mg daily of simvastatin. (7.2)

8 USE IN SPECIFIC POPULATIONS

- Pediatric: Effect on patients less than 6 years old is not known. (8.4)
- Geriatric: Start dosing at the low end of the dose range. (8.5)
- Hepatic Impairment: Start dosing at the low end of the dose range. (8.6)

FULL PRESCRIBING INFORMATION

1 INDICATIONS AND USAGE

1.1 Hypertension

NORLIQVA® is indicated for the treatment of hypertension, to lower blood pressure in adults and children 6 years of age and older. Lowering blood pressure reduces the risk of fatal and nonfatal cardiovascular events, primarily strokes and myocardial infarctions. These benefits have been seen in controlled trials of antihypertensive drugs from a wide variety of pharmacologic classes including NORLIQVA.

Control of high blood pressure should be part of comprehensive cardiovascular risk management, including, as appropriate, lipid control, diabetes management, antithrombotic therapy, smoking cessation, exercise, and limited sodium intake. Many patients will require more than one drug to achieve blood pressure goals. For specific advice on goals and management, see published guidelines, such as those of the National High Blood Pressure Education Program's Joint National Committee on Prevention, Detection, Evaluation, and Treatment of High Blood Pressure (JNC).

Numerous antihypertensive drugs, from a variety of pharmacologic classes and with different mechanisms of action, have been shown in randomized controlled trials to reduce cardiovascular morbidity and mortality, and it can be concluded that it is blood pressure reduction, and not some other pharmacologic property of the drugs, that is largely responsible for those benefits. The largest and most consistent cardiovascular outcome benefit has been a reduction in the risk of stroke, but reductions in myocardial infarction and cardiovascular mortality also have been seen regularly.

Elevated systolic or diastolic pressure causes increased cardiovascular risk, and the absolute risk increase per mmHg is greater at higher blood pressures, so that even modest reductions of severe hypertension can provide substantial benefit. Relative risk reduction from blood pressure reduction is similar across populations with varying absolute risk, so the absolute benefit is greater in patients who are at higher risk independent of their hypertension (for example, patients with diabetes or hyperlipidemia), and such patients would be expected to benefit from more aggressive treatment to a lower blood pressure goal.

Some antihypertensive drugs have smaller blood pressure effects (as monotherapy) in black patients, and many antihypertensive drugs have additional approved indications and effects (e.g., on angina, heart failure, or diabetic kidney disease). These considerations may guide selection of therapy.

NORLIQVA may be used alone or in combination with other antihypertensive agents.

1.2 Coronary Artery Disease (CAD)

Chronic Stable Angina
NORLIQVA is indicated for the symptomatic treatment of chronic stable angina. NORLIQVA may be used alone or in combination with other antianginal agents.

Vasospastic Angina (Prinzmetal's or Variant Angina)
NORLIQVA is indicated for the treatment of confirmed or suspected vasospastic angina.
NORLIQVA may be used as monotherapy or in combination with other antianginal agents.

Angiographically Documented CAD
In patients with recently documented CAD by angiography and without heart failure or an ejection fraction <40%, NORLIQVA is indicated to reduce the risk of hospitalization for angina and to reduce the risk of a coronary revascularization procedure.

2 DOSAGE AND ADMINISTRATION

2.1 Adults

The usual initial antihypertensive oral dose of NORLIQVA is 5 mg orally once daily, and the maximum dose is 10 mg orally once daily.

Small, fragile, or elderly patients, or patients with hepatic insufficiency may be started on 2.5 mg orally once daily and this dose may be used when adding NORLIQVA to other antihypertensive therapy [see Clinical Pharmacology (12.3)].

Adjust dosage according to blood pressure goals. In general, wait 7 to 14 days between titration steps. Titrate more rapidly, however, if clinically warranted, provided the patient is assessed frequently.

Angina: The recommended dose for chronic stable or vasospastic angina is 5 mg to 10 mg orally once daily, with the lower dose suggested in the elderly and in patients with hepatic insufficiency. Most patients will require 10 mg orally once daily for adequate effect.

Coronary artery disease: The recommended dose range for patients with coronary artery disease is 5 mg to 10 mg orally once daily. In clinical studies, the majority of patients required 10 mg [see Clinical Studies (14.4)].

2.2 Children

The effective antihypertensive oral dose in pediatric patients ages 6 years of age and older is 2.5 mg to 5 mg orally once daily. Doses in excess of 5 mg daily have not been studied in pediatric patients [see Clinical Pharmacology (12.4), Clinical Studies (14.1)].

3 DOSAGE FORMS AND STRENGTHS

Oral Solution: 1 mg/mL clear, pale straw-colored solution with a mixed berry flavor.

4 CONTRAINDICATIONS

NORLIQVA is contraindicated in patients with sensitivity to amlodipine.

5 WARNINGS AND PRECAUTIONS

5.1 Hypotension

Symptomatic hypotension is possible, particularly in patients with severe aortic stenosis. Because of the gradual onset of action, acute hypotension is unlikely.

5.2 Increased Angina or Myocardial Infarction

Worsening angina and acute myocardial infarction can develop after starting or increasing the dose of NORLIQVA, particularly in patients with severe obstructive coronary artery disease.

5.3 Patients with Hepatic Failure

Because amlodipine is extensively metabolized by the liver and the plasma elimination half-life (t1/2) is 56 hours in patients with impaired hepatic function, titrate slowly when administering NORLIQVA to patients with severe hepatic impairment.

6 ADVERSE REACTIONS

6.1 Clinical Trials Experience

Because clinical trials are conducted under widely varying conditions, adverse reaction rates observed in the clinical trials of a drug cannot be directly compared to rates in the clinical trials of another drug and may not reflect the rates observed in practice.

Amlodipine has been evaluated for safety in more than 11,000 patients in U.S. and foreign clinical trials. In general, treatment with amlodipine was well-tolerated at doses up to 10 mg daily. Most adverse reactions reported during therapy with amlodipine were of mild or moderate severity. In controlled clinical trials directly comparing amlodipine (N=1730) at doses up to 10 mg to placebo (N=1250), discontinuation of amlodipine because of adverse reactions was required in only about 1.5% of patients and was not significantly different from placebo (about 1%). The most commonly reported adverse reactions more frequent than placebo are reflected in the table below. The incidence (%) of adverse reactions that occurred in a dose-related manner are as follows:

 | Amlodipine |  |  | Placebo
 | 2.5 mg N=275 | 5 mg N=296 | 10 mg N=268 | N=520
Edema | 1.8 | 3.0 | 10.8 | 0.6
Dizziness | 1.1 | 3.4 | 3.4 | 1.5
Flushing | 0.7 | 1.4 | 2.6 | 0.0
Palpitation | 0.7 | 1.4 | 4.5 | 0.6

Other adverse reactions that were not clearly dose-related but were reported include:

 | Amlodipine (%) (N=1730) | Placebo (%) (N=1250)
Fatigue | 4.5 | 2.8
Nausea | 2.9 | 1.9

For several adverse reactions that appear to be drug and dose related, there was a greater incidence in women than men associated with amlodipine treatment as shown in the following table:

 | Amlodipine |  | Placebo
 | Male=% (N=1218) | Female=% (N=512) | Male=% (N=914) | Female=% (N=336)
Edema | 5.6 | 14.6 | 1.4 | 5.1
Flushing | 1.5 | 4.5 | 0.3 | 0.9
Palpitations | 1.4 | 3.3 | 0.9 | 0.9
Somnolence | 1.3 | 1.6 | 0.8 | 0.3

6.2 Postmarketing Experience

Because these reactions are reported voluntarily from a population of uncertain size, it is not always possible to reliably estimate their frequency or establish a causal relationship to drug exposure.

General: gynecomastia

Hepatic: jaundice and hepatic enzyme elevations, some requiring hospitalization

Neurologic: extrapyramidal disorder

7 DRUG INTERACTIONS

7.1 Impact of Other Drugs on Amlodipine

CYP3A Inhibitors
Co-administration with CYP3A inhibitors (moderate and strong) results in increased systemic exposure to amlodipine and may require dose reduction. Monitor for symptoms of hypotension and edema when amlodipine is co-administered with CYP3A inhibitors to determine the need for dose adjustment [see Clinical Pharmacology (12.3)].

CYP3A Inducers
No information is available on the quantitative effects of CYP3A inducers on amlodipine. Blood pressure should be closely monitored when amlodipine is co-administered with CYP3A inducers.

7.2 Impact of Amlodipine on Other Drugs

Simvastatin
Co-administration of simvastatin with amlodipine increases the systemic exposure of simvastatin. Limit the dose of simvastatin in patients on amlodipine to 20 mg daily [see Clinical Pharmacology (12.3)].

Immunosuppressants
Amlodipine may increase the systemic exposure of cyclosporine or tacrolimus when co-administered. Frequent monitoring of trough blood levels of cyclosporine and tacrolimus is recommended and adjust the dose when appropriate [see Clinical Pharmacology (12.3)].

8 USE IN SPECIFIC POPULATIONS

8.1 Pregnancy

Risk Summary:
The limited available data based on post-marketing reports with amlodipine use in pregnant women are not sufficient to inform a drug-associated risk for major birth defects and miscarriage. There are risks to the mother and fetus associated with poorly controlled hypertension in pregnancy [see Clinical Considerations] In animal reproduction studies, there was no evidence of adverse developmental effects when pregnant rats and rabbits were treated orally with amlodipine maleate during organogenesis at doses approximately 10 and 20-times the maximum recommended human dose (MRHD), respectively. However for rats, litter size was significantly decreased (by about 50%) and the number of intrauterine deaths was significantly increased (about 5-fold). Amlodipine has been shown to prolong both the gestation period and the duration of labor in rats at this dose [see Data].

The estimated background risk of major birth defects and miscarriage for the indicated population is unknown. All pregnancies have a background risk of birth defect, loss or other adverse outcomes. In the U.S. general population, the estimated background risk of major birth defects and miscarriage in clinically recognized pregnancies is 2%–4% and 15%–20%, respectively.

Clinical Considerations
Disease-associated maternal and/or embryo/fetal risk
Hypertension in pregnancy increases the maternal risk for pre-eclampsia, gestational diabetes, premature delivery, and delivery complications (e.g., need for cesarean section and post-partum hemorrhage). Hypertension increases the fetal risk for intrauterine growth restriction and intrauterine death. Pregnant women with hypertension should be carefully monitored and managed accordingly.

Data
Animal Data
No evidence of teratogenicity was found when pregnant rats and rabbits were treated orally with amlodipine maleate at doses up to 10 mg amlodipine/kg/day (approximately 10 and 20 times the MRHD based on body surface area, respectively) during their respective periods of major organogenesis. However for rats, litter size was significantly decreased (by about 50%) and the number of intrauterine deaths was significantly increased (about 5-fold) in rats receiving amlodipine maleate at a dose equivalent to 10 mg amlodipine/kg/day for 14 days before mating and throughout mating and gestation. Amlodipine maleate has been shown to prolong both the gestation period and the duration of labor in rats at this dose.

8.2 Lactation

Risk Summary
Limited available data from a published clinical lactation study reports that amlodipine is present in human milk at an estimated median relative infant dose of 4.2%. No adverse effects of amlodipine on the breastfed infant have been observed. There is no available information on the effects of amlodipine on milk production.

8.4 Pediatric Use

Amlodipine (2.5 to 5 mg daily) is effective in lowering blood pressure in patients 6 years of age and older [see Clinical Studies (14.1)].

Effect of amlodipine on blood pressure in patients less than 6 years of age is not known.

8.5 Geriatric Use

Clinical studies of amlodipine did not include sufficient numbers of subjects aged 65 and over to determine whether they respond differently from younger subjects. Other reported clinical experience has not identified differences in responses between the elderly and younger patients. In general, dose selection for an elderly patient should be cautious, usually starting at the low end of the dosing range, reflecting the greater frequency of decreased hepatic, renal, or cardiac function, and of concomitant disease or other drug therapy. Elderly patients have decreased clearance of amlodipine with a resulting increase of AUC of approximately 40–60%, and a lower initial dose may be required [see Dosage and Administration (2.1)].

8.6 Hepatic Impairment

Patients with hepatic impairment have reduced clearance of amlodipine with a resulting increase of AUC. A lower initial dose may be required [see Dosage and Administration (2.1)].

10 OVERDOSAGE

Overdosage might be expected to cause excessive peripheral vasodilation with marked hypotension and possibly a reflex tachycardia.

Single oral doses of amlodipine maleate equivalent to 40 mg amlodipine/kg and 100 mg amlodipine/kg in mice and rats, respectively, caused deaths. Single oral amlodipine maleate doses equivalent to 4 or more mg amlodipine/kg or higher in dogs (11 or more times the maximum recommended human dose on a mg/m^2 basis) caused a marked peripheral vasodilation and hypotension.

If massive overdose should occur, initiate active cardiac and respiratory monitoring. Frequent blood pressure measurements are essential. Should hypotension occur, provide cardiovascular support including elevation of the extremities and the judicious administration of fluids. If hypotension remains unresponsive to these conservative measures, consider administration of vasopressors (such as phenylephrine) with attention to circulating volume and urine output. As amlodipine is highly protein bound, hemodialysis is not likely to be of benefit.

11 DESCRIPTION

NORLIQVA is the besylate salt of amlodipine, a long-acting calcium channel blocker.

Amlodipine besylate is chemically described as 3-Ethyl-5-methyl (±)-2-[(2-aminoethoxy)methyl]-4-(2-chlorophenyl)-1,4-dihydro-6-methyl-3,5-pyridinedicarboxylate, monobenzenesulphonate. Its empirical formula is C20H25CIN2O5•C6H6O3S, and its structural formula is:

Amlodipine besylate is a white crystalline powder with a molecular weight of 567.1. It is slightly soluble in water and sparingly soluble in ethanol. Each mL of NORLIQVA (amlodipine) oral solution contains 1 mg of amlodipine provided as 1.385 mg of amlodipine besylate and the following inactive ingredients: butylated hydroxyanisole, glycerin, propylene glycol and mixed berry flavor.

12 CLINICAL PHARMACOLOGY

12.1 Mechanism of Action

Amlodipine is a dihydropyridine calcium antagonist (calcium ion antagonist or slow-channel blocker) that inhibits the transmembrane influx of calcium ions into vascular smooth muscle and cardiac muscle. Experimental data suggest that amlodipine binds to both dihydropyridine and nondihydropyridine binding sites. The contractile processes of cardiac muscle and vascular smooth muscle are dependent upon the movement of extracellular calcium ions into these cells through specific ion channels. Amlodipine inhibits calcium ion influx across cell membranes selectively, with a greater effect on vascular smooth muscle cells than on cardiac muscle cells. Negative inotropic effects can be detected in vitro but such effects have not been seen in intact animals at therapeutic doses. Serum calcium concentration is not affected by amlodipine. Within the physiologic pH range, amlodipine is an ionized compound (pKa=8.6), and its kinetic interaction with the calcium channel receptor is characterized by a gradual rate of association and dissociation with the receptor binding site, resulting in a gradual onset of effect.

Amlodipine is a peripheral arterial vasodilator that acts directly on vascular smooth muscle to cause a reduction in peripheral vascular resistance and reduction in blood pressure.

The precise mechanisms by which amlodipine relieves angina have not been fully delineated, but are thought to include the following:

Exertional Angina: In patients with exertional angina, amlodipine reduces the total peripheral resistance (afterload) against which the heart works and reduces the rate pressure product, and thus myocardial oxygen demand, at any given level of exercise.

Vasospastic Angina: Amlodipine has been demonstrated to block constriction and restore blood flow in coronary arteries and arterioles in response to calcium, potassium epinephrine, serotonin, and thromboxane A2 analog in experimental animal models and in human coronary vessels in vitro. This inhibition of coronary spasm is responsible for the effectiveness of amlodipine in vasospastic (Prinzmetal's or variant) angina.

12.2 Pharmacodynamics

Hemodynamics: Following administration of therapeutic doses to patients with hypertension, amlodipine produces vasodilation resulting in a reduction of supine and standing blood pressures. These decreases in blood pressure are not accompanied by a significant change in heart rate or plasma catecholamine levels with chronic dosing. Although the acute intravenous administration of amlodipine decreases arterial blood pressure and increases heart rate in hemodynamic studies of patients with chronic stable angina, chronic oral administration of amlodipine in clinical trials did not lead to clinically significant changes in heart rate or blood pressures in normotensive patients with angina.

With chronic once daily oral administration, antihypertensive effectiveness is maintained for at least 24 hours. Plasma concentrations correlate with effect in both young and elderly patients. The magnitude of reduction in blood pressure with amlodipine is also correlated with the height of pretreatment elevation; thus, individuals with moderate hypertension (diastolic pressure 105-114 mmHg) had about a 50% greater response than patients with mild hypertension (diastolic pressure 90–104 mmHg). Normotensive subjects experienced no clinically significant change in blood pressures (+1/–2 mmHg).

In hypertensive patients with normal renal function, therapeutic doses of amlodipine resulted in a decrease in renal vascular resistance and an increase in glomerular filtration rate and effective renal plasma flow without change in filtration fraction or proteinuria.

As with other calcium channel blockers, hemodynamic measurements of cardiac function at rest and during exercise (or pacing) in patients with normal ventricular function treated with amlodipine have generally demonstrated a small increase in cardiac index without significant influence on dP/dt or on left ventricular end diastolic pressure or volume. In hemodynamic studies, amlodipine has not been associated with a negative inotropic effect when administered in the therapeutic dose range to intact animals and man, even when co-administered with beta-blockers to man. Similar findings, however, have been observed in normal or well-compensated patients with heart failure with agents possessing significant negative inotropic effects.

Electrophysiologic Effects: Amlodipine does not change sinoatrial nodal function or atrioventricular conduction in intact animals or man. In patients with chronic stable angina, intravenous administration of 10 mg did not significantly alter A-H and H-V conduction and sinus node recovery time after pacing. Similar results were obtained in patients receiving amlodipine and concomitant beta-blockers. In clinical studies in which amlodipine was administered in combination with beta-blockers to patients with either hypertension or angina, no adverse effects on electrocardiographic parameters were observed. In clinical trials with angina patients alone, amlodipine therapy did not alter electrocardiographic intervals or produce higher degrees of AV blocks.

12.3 Pharmacokinetics

Absorption
Amlodipine reaches peak plasma concentration (Cmax) within 6.5 hours following oral administration of NORLIQVA. Absolute bioavailability of amlodipine has been estimated to be between 64 and 90%.

Effect of food
Administration with a high- fat, high-calorie meal did not have a significant effect on the Cmax and AUC of NORLIQVA.

Distribution
Ex vivo studies have shown that approximately 93% of the circulating drug is bound to plasma proteins in hypertensive patients. Steady-state plasma levels of amlodipine are reached after 7 to 8 days of consecutive daily dosing.

Elimination
Metabolism
Amlodipine is extensively (about 90%) converted to inactive metabolites via hepatic metabolism with 10% of the parent compound and 60% of the metabolites excreted in the urine

Excretion
Elimination from the plasma is biphasic with a mean terminal elimination half-life of 52 hours.

Specific Populations
Geriatric Patients
The renal clearance of amlodipine is lower in elderly patients compared to younger adults. This results in increase in AUC of approximately 40-60% [see Dosage & Administration (2.1)].

Pediatric Patients
Sixty-two hypertensive patients aged 6 to 17 years received doses of amlodipine between 1.25 mg and 20 mg. Weight-adjusted clearance and volume of distribution were similar to values in adults.

Patients with Renal Impairment
The pharmacokinetics of amlodipine is not significantly influenced by renal impairment. Patients with renal failure may therefore receive the usual initial dose.

Patients with Hepatic Impairment
Patients with hepatic impairment have reduced clearance of amlodipine with a resulting increase in the AUC of approximately 40-60% [see Dosage and Administration (2.1)].

Patients with Heart Failure
Approximately 40-60% increase in AUC was observed in patients with moderate to severe heart failure.

Drug Interaction Studies
In vitro data indicate that amlodipine has no effect on the human plasma protein binding of digoxin, phenytoin, warfarin, and indomethacin.

Impact of other drugs on amlodipine
Co-administered cimetidine, magnesium-and aluminum hydroxide antacids, sildenafil, and grapefruit juice have no impact on the exposure to amlodipine.

CYP3A inhibitors: Co-administration of a 180 mg daily dose of diltiazem with 5 mg amlodipine in elderly hypertensive patients resulted in a 60% increase in amlodipine systemic exposure. Erythromycin co-administration in healthy volunteers did not significantly change amlodipine systemic exposure. However, strong inhibitors of CYP3A (e.g., itraconazole, clarithromycin) may increase the plasma concentrations of amlodipine to a greater extent [see Drug Interactions (7.1)].

Impact of amlodipine on other drugs
Amlodipine is a weak inhibitor of CYP3A and may increase exposure to CYP3A substrates.

Co-administered amlodipine does not affect the exposure to atorvastatin, digoxin, ethanol and the warfarin prothrombin response time.

Simvastatin

Co-administration of multiple doses of 10 mg of amlodipine with 80 mg simvastatin resulted in a 77% increase in exposure to simvastatin compared to simvastatin alone [see Drug Interactions (7.2)].

Cyclosporine

A prospective study in renal transplant patients (N=11) showed on an average of 40% increase in trough cyclosporine levels when concomitantly treated with amlodipine [see Drug Interactions (7.2)].

Tacrolimus

A prospective study in healthy Chinese volunteers (N=9) with CYP3A5 expressers showed 2.5- to 4-fold the exposure to tacrolimus when concomitantly administered with amlodipine compared to tacrolimus alone. This finding was not observed in CYP3A5 non-expressers (N= 6). However, 3-fold the plasma exposure to tacrolimus was seen in a renal transplant patient (CYP3A5 non-expresser) upon initiation of amlodipine for the treatment of post-transplant hypertension. Irrespective of the CYP3A5 genotype status, the possibility of an interaction cannot be excluded with these drugs [see Drug Interactions (7.2)].

13 NONCLINICAL TOXICOLOGY

13.1 Carcinogenesis, Mutagenesis, Impairment of Fertility

Rats and mice treated with amlodipine maleate in the diet for up to two years, at concentrations calculated to provide daily dosage levels of amlodipine 0.5, 1.25, and 2.5 mg/kg/day, showed no evidence of a carcinogenic effect of the drug. For the mouse, the highest dose was, on a mg/m^2 basis, similar to the maximum recommended human dose of 10 mg amlodipine/day.^1 For the rat, the highest dose was, on a mg/m^2 basis, about twice the maximum recommended human dose.^1

Mutagenicity studies conducted with amlodipine maleate revealed no drug related effects at either the gene or chromosome level.

There was no effect on the fertility of rats treated orally with amlodipine maleate (males for 64 days and females for 14 days prior to mating) at doses up to 10 mg amlodipine/kg/day (8 times the maximum recommended human dose^1 of 10 mg/day on a mg/m^2 basis).

^1 Based on patient weight of 50 kg

14 CLINICAL STUDIES

14.1 Effects in Hypertension

Adult Patients
The antihypertensive efficacy of amlodipine has been demonstrated in a total of 15 double-blind, placebo-controlled, randomized studies involving 800 patients on amlodipine and 538 on placebo. Once daily administration produced statistically significant placebo-corrected reductions in supine and standing blood pressures at 24 hours postdose, averaging about 12/6 mmHg in the standing position and 13/7 mmHg in the supine position in patients with mild to moderate hypertension. Maintenance of the blood pressure effect over the 24-hour dosing interval was observed, with little difference in peak and trough effect. Tolerance was not demonstrated in patients studied for up to 1 year. The 3 parallel, fixed dose, dose response studies showed that the reduction in supine and standing blood pressures was dose-related within the recommended dosing range. Effects on diastolic pressure were similar in young and older patients. The effect on systolic pressure was greater in older patients, perhaps because of greater baseline systolic pressure. Effects were similar in black patients and in white patients.

Pediatric Patients
Two hundred sixty-eight hypertensive patients aged 6 to 17 years were randomized first to amlodipine 2.5 or 5 mg once daily for 4 weeks and then randomized again to the same dose or to placebo for another 4 weeks. Patients receiving 2.5 mg or 5 mg at the end of 8 weeks had significantly lower systolic blood pressure than those secondarily randomized to placebo. The magnitude of the treatment effect is difficult to interpret, but it is probably less than 5 mmHg systolic on the 5 mg dose and 3.3 mmHg systolic on the 2.5 mg dose. Adverse events were similar to those seen in adults.

14.2 Effects in Chronic Stable Angina

The effectiveness of 5–10 mg/day of amlodipine in exercise-induced angina has been evaluated in 8 placebo-controlled, double-blind clinical trials of up to 6 weeks duration involving 1038 patients (684 amlodipine, 354 placebo) with chronic stable angina. In 5 of the 8 studies, significant increases in exercise time (bicycle or treadmill) were seen with the 10 mg dose. Increases in symptom-limited exercise time averaged 12.8% (63 sec) for amlodipine 10 mg, and averaged 7.9% (38 sec) for amlodipine 5 mg. amlodipine 10 mg also increased time to 1 mm ST segment deviation in several studies and decreased angina attack rate. The sustained efficacy of amlodipine in angina patients has been demonstrated over long-term dosing. In patients with angina, there were no clinically significant reductions in blood pressures (4/1 mmHg) or changes in heart rate (+0.3 bpm).

14.3 Effects in Vasospastic Angina

In a double-blind, placebo-controlled clinical trial of 4 weeks duration in 50 patients, amlodipine therapy decreased attacks by approximately 4/week compared with a placebo decrease of approximately 1/week (p<0.01). Two of 23 amlodipine and 7 of 27 placebo patients discontinued from the study due to lack of clinical improvement.

14.4 Effects in Documented Coronary Artery Disease

In PREVENT, 825 patients with angiographically documented coronary artery disease were randomized to amlodipine (5–10 mg once daily) or placebo and followed for 3 years. Although the study did not show significance on the primary objective of change in coronary luminal diameter as assessed by quantitative coronary angiography, the data suggested a favorable outcome with respect to fewer hospitalizations for angina and revascularization procedures in patients with CAD.

CAMELOT enrolled 1318 patients with CAD recently documented by angiography, without left main coronary disease and without heart failure or an ejection fraction <40%. Patients (76% males, 89% Caucasian, 93% enrolled at US sites, 89% with a history of angina, 52% without PCI, 4% with PCI and no stent, and 44% with a stent) were randomized to double-blind treatment with either amlodipine (5–10 mg once daily) or placebo in addition to standard care that included aspirin (89%), statins (83%), beta-blockers (74%), nitroglycerin (50%), anti-coagulants (40%), and diuretics (32%), but excluded other calcium channel blockers. The mean duration of follow-up was 19 months. The primary endpoint was the time to first occurrence of one of the following events: hospitalization for angina pectoris, coronary revascularization, myocardial infarction, cardiovascular death, resuscitated cardiac arrest, hospitalization for heart failure, stroke/TIA, or peripheral vascular disease. A total of 110 (16.6%) and 151 (23.1%) first events occurred in the amlodipine and placebo groups, respectively, for a hazard ratio of 0.691 (95% CI: 0.540–0.884, p = 0.003). The primary endpoint is summarized in Figure 1 below. The outcome of this study was largely derived from the prevention of hospitalizations for angina and the prevention of revascularization procedures (see Table 1). Effects in various subgroups are shown in Figure 2.

In an angiographic substudy (n=274) conducted within CAMELOT, there was no significant difference between amlodipine and placebo on the change of atheroma volume in the coronary artery as assessed by intravascular ultrasound.

Figure 1 - Kaplan-Meier Analysis of Composite Clinical Outcomes for Amlodipine versus Placebo

Figure 2 – Effects on Primary Endpoint of Amlodipine versus Placebo across Sub-Groups

Table 1 below summarizes the significant composite endpoint and clinical outcomes from the composites of the primary endpoint. The other components of the primary endpoint including cardiovascular death, resuscitated cardiac arrest, myocardial infarction, hospitalization for heart failure, stroke/TIA, or peripheral vascular disease did not demonstrate a significant difference between amlodipine and placebo.

Table 1 – Incidence of Significant Clinical Outcomes for CAMELOT

Clinical Outcomes N (%) | Amlodipine (N=663) | Placebo (N=655) | Risk Reduction (p-value)
Composite CV Endpoint | 110 (16.6) | 151 (23.1) | 31% (0.003)
Hospitalization for Angina* | 51 (7.7) | 84 (12.8) | 42% (0.002)
Coronary Revascularization* | 78 (11.8) | 103 (15.7) | 27% (0.033)

* Total patients with these events

14.5 Studies in Patients with Heart Failure

Amlodipine has been compared to placebo in four 8–12 week studies of patients with NYHA Class II/III heart failure, involving a total of 697 patients. In these studies, there was no evidence of worsened heart failure based on measures of exercise tolerance, NYHA classification, symptoms, or left ventricular ejection fraction. In a long-term (follow-up at least 6 months, mean 13.8 months) placebo-controlled mortality/morbidity study of amlodipine 5–10 mg in 1153 patients with NYHA Classes III (n=931) or IV (n=222) heart failure on stable doses of diuretics, digoxin, and ACE inhibitors, amlodipine had no effect on the primary endpoint of the study which was the combined endpoint of all-cause mortality and cardiac morbidity (as defined by life-threatening arrhythmia, acute myocardial infarction, or hospitalization for worsened heart failure), or on NYHA classification, or symptoms of heart failure. Total combined all-cause mortality and cardiac morbidity events were 222/571 (39%) for patients on amlodipine and 246/583 (42%) for patients on placebo; the cardiac morbid events represented about 25% of the endpoints in the study.

Another study (PRAISE-2) randomized patients with NYHA Class III (80%) or IV (20%) heart failure without clinical symptoms or objective evidence of underlying ischemic disease, on stable doses of ACE inhibitors (99%), digitalis (99%), and diuretics (99%), to placebo (n=827) or amlodipine (n=827) and followed them for a mean of 33 months. There was no statistically significant difference between amlodipine and placebo in the primary endpoint of all-cause mortality (95% confidence limits from 8% reduction to 29% increase on amlodipine). With amlodipine there were more reports of pulmonary edema.

16 HOW SUPPLIED/STORAGE AND HANDLING

NORLIQVA (amlodipine) oral solution, 1 mg/mL is a clear, pale straw-colored solution with a mixed berry flavor supplied in 150 mL white HDPE bottles with a child-resistant closure.

NDC 46287-037-01

Storage

Store at 20°C to 25°C (68°F to 77°F); excursion permitted to 15°C to 30°C (59°F to 86°F) [see USP Controlled Room Temperature]. Dispense in light-resistant and tight (per USP) container.

Distributed by CMP Pharma, Inc., Farmville, NC 27828

NORLIQVA is a registered trademark of CMP Development LLC.

3097 R0226

Principal Display Panel - 150 mL Bottle Label

Alcohol Free

150 mL

Rx Only

NDC 46287-037-01

Norliqva®

(Amlodipine) Oral Solution
1 mg/mL

FOR ORAL USE ONLY